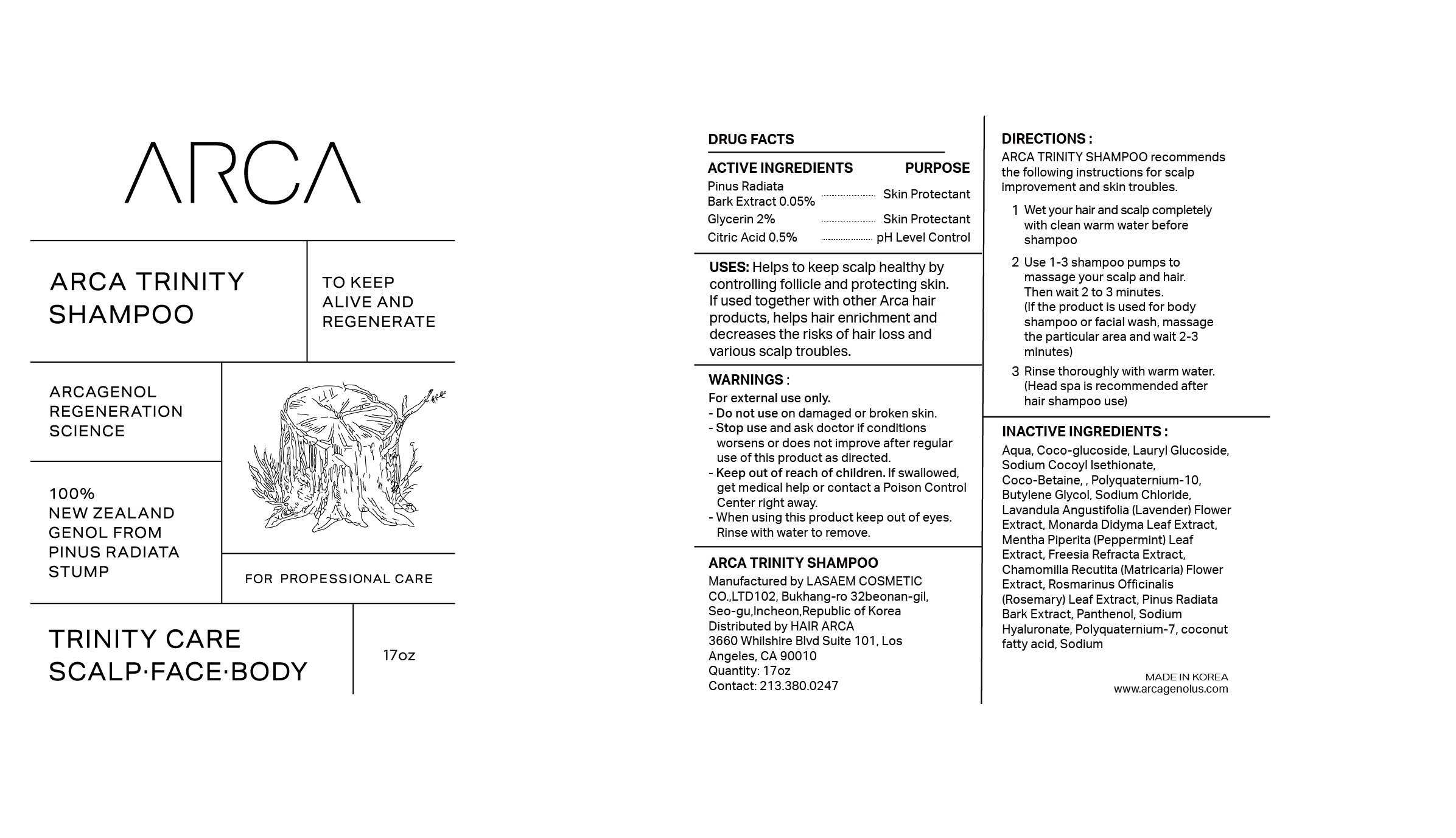 DRUG LABEL: ARCA TRINITYSHAMPOO
NDC: 83104-501 | Form: SHAMPOO
Manufacturer: Hair Arca, Inc
Category: otc | Type: HUMAN OTC DRUG LABEL
Date: 20221004

ACTIVE INGREDIENTS: PINUS RADIATA BARK 0.05 g/100 mL; GLYCERIN 2 g/100 mL; CITRIC ACID MONOHYDRATE 0.5 g/100 mL
INACTIVE INGREDIENTS: BUTYLENE GLYCOL; CHAMOMILE; HYALURONIC ACID; HYALURONATE SODIUM; WATER; SODIUM COCOYL ISETHIONATE; MONARDA DIDYMA LEAF; COCO-BETAINE; SODIUM CHLORIDE; MENTHA PIPERITA LEAF; POLYQUATERNIUM-7 (70/30 ACRYLAMIDE/DADMAC; 1600 KD); SODIUM; LAVANDULA ANGUSTIFOLIA FLOWERING TOP; FREESIA ALBA FLOWER; PANTHENOL; COCONUT ACID; ROSEMARY; LAURYL GLUCOSIDE; POLYQUATERNIUM-10 (400 CPS AT 2%); COCO GLUCOSIDE

83104-501 ARCA Trinity Shampoo

Active ingredients

Pinus Radiata Bark Extract 0.05%
Glycerin 2%
Citric Acid 0.5%

Purposes

Pinus Radiata Bark Extract 0.05% - Skin Protectant
Glycerin 2% - Skin Protectant
Citric Acid 0.5% - pH Level Control

Uses

Helps to keep scalp healthy by controlling follicle and protecting skin.
If used together with other Arca hair products, helps hair enrichment and decreases the risks of hair loss and various scalp troubles.

Warnings

For external use only.

Warnings

When using this product keep out of eyes.
Rinse with water to remove.

Warnings

Stop use and ask doctor if conditions worsens or does not improve after regular use of this product as directed.

Warnings

Keep out of reach of children. If swallowed, get medical help or contact a Poison Control Center right away.

Warnings

Do not use on damaged or broken skin.

Directions

ARCA TRINITY SHAMPOO recommends the following instructions for scalp
improvement and skin troubles.

1 Wet your hair and scalp completely with clean warm water before shampoo
2 Use 1-3 shampoo pumps to massage your scalp and hair.
Then wait 2 to 3 minutes.
(If the product is used for body shampoo or facial wash, massage the particular area and wait 2-3 minutes)
3 Rinse thoroughly with warm water.
(Head spa is recommended after hair shampoo use)

Inactive ingredients

Aqua, Coco-glucoside, Lauryl Glucoside, Sodium Cocoyl Isethionate, Coco-Betaine, Polyquaternium-10, Butylene Glycol, Sodium Chloride, Lavandula Angustifolia (Lavender) Flower Extract, Monarda Didyma Leaf Extract, Mentha Piperita (Peppermint) Leaf Extract,
Freesia Refracta Extract, Chamomilla Recutita (Matricaria) Flower Extract, Rosmarinus Officinalis (Rosemary) Leaf Extract, Pinus Radiata Bark Extract, Panthenol, Sodium Hyaluronate, Polyquaternium-7, coconut fatty acid, Sodium

Display Panel

83104-501